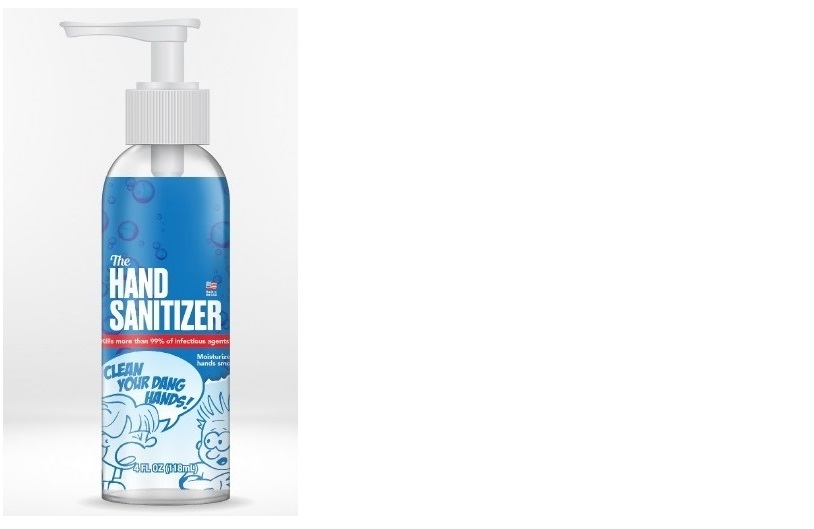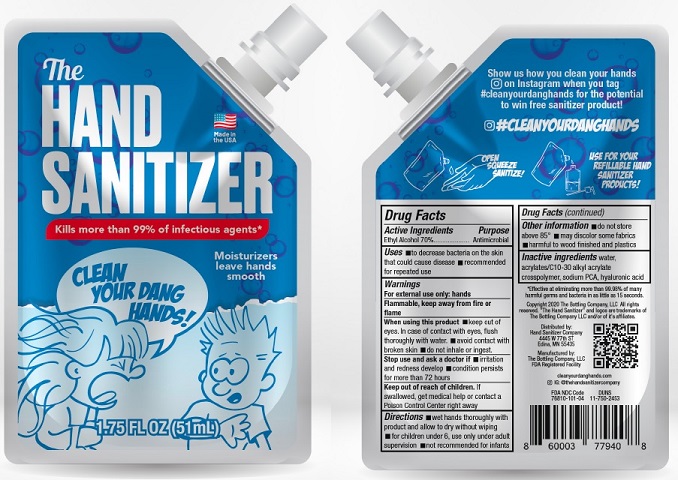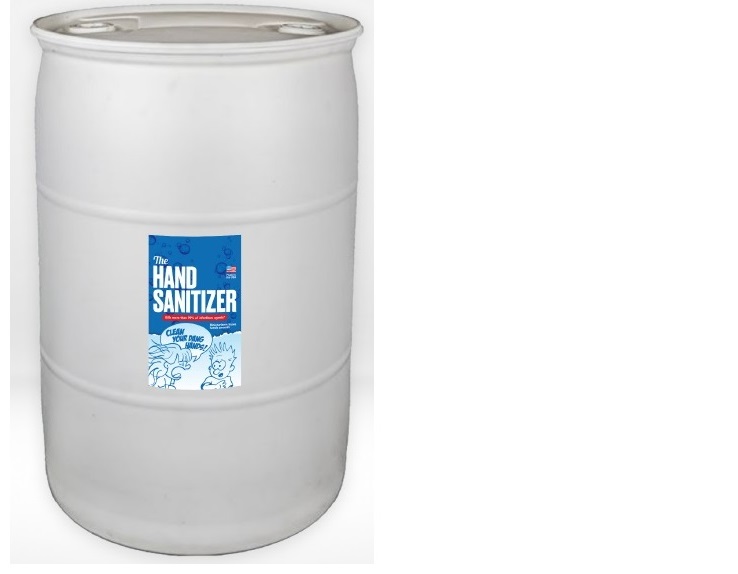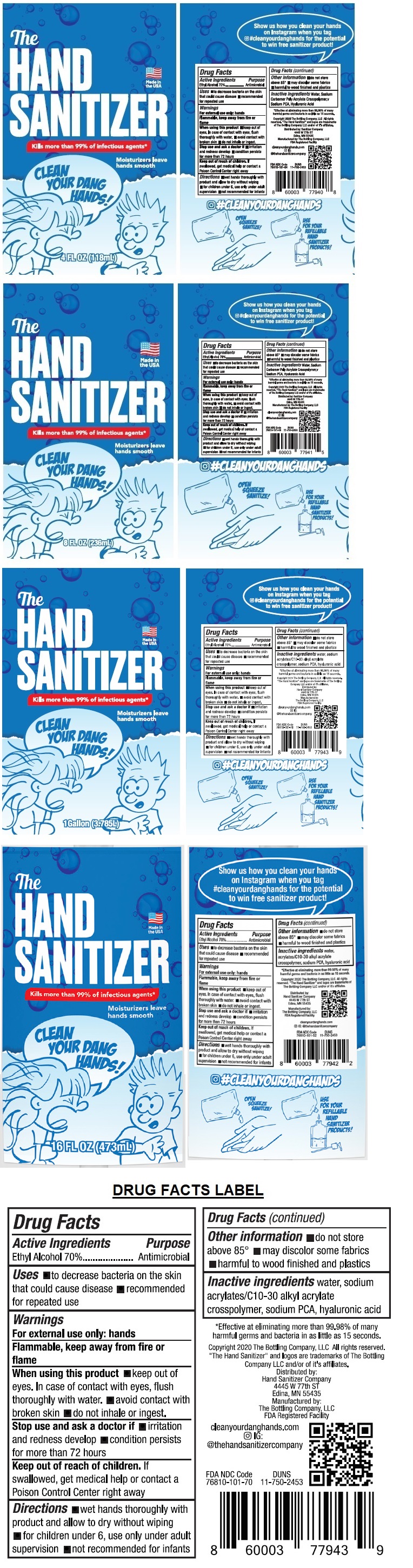 DRUG LABEL: Hand Sanitizer
NDC: 76810-101 | Form: LIQUID
Manufacturer: Hand Sanitizer Company LLC
Category: otc | Type: HUMAN OTC DRUG LABEL
Date: 20200807

ACTIVE INGREDIENTS: ALCOHOL 70 mL/100 mL
INACTIVE INGREDIENTS: WATER; SODIUM POLYACRYLATE (8000 MW); SODIUM PYRROLIDONE CARBOXYLATE; HYALURONIC ACID

The Hand Sanitizer

Active Ingredients

Ethyl Alcohol 70%

Purpose

Antimicrobial

INDICATIONS AND USAGE

Uses ■ to decrease bacteria on the skin that could cause disease ■ recommended for repeated use

Warnings

For external use only: hands

Flammable, keep away from fire or flame

When using this product ■ keep out of eyes. In case of contact with eyes, flush thoroughly with water. ■ avoid contact with broken skin ■ do not inhale or ingest.

Stop use and ask a doctor if ■ irritation and redness develop ■ condition persists for more than 72 hours

Keep out of reach of children. If swallowed, get medical help or contact a Poison Control Center right away

DOSAGE AND ADMINISTRATION

Directions ■ wet hands thoroughly with product and allow to dry without wiping ■ for children under 6, use only under adult supervision ■ not recommended for infants

Other information ■ do not store above 85°F ■ may discolor some fabrics ■ harmful to wood finishes and plastics

INACTIVE INGREDIENT

Inactive ingredients water, sodium acrylates/C10-30 alkyl acrylate crosspolymer, sodium PCA, hyaluronic acid

Made in the USA

Kills more than 99% of infectious agents*

Moisturizers leave hands smooth

CLEAN YOUR DANG HANDS!

Show us how you clean your hands on Instagram when you tag #cleanyourdanghands for the potential to win free sanitizer product!

*Effective at eliminating more than 99.98% of many harmful germs and bacteria in as little as 15 seconds.

Copyright 2020 The Bottling Company, LLC All rights reserved. "The Hand Sanitizer" and logos are trademarks of The Bottling Company LLC and/or of it’s affiliates.

Distributed by: Sanitizer Company

4445 W 77th ST

Edina, MN 55435

Manufactured by: The Bottling Company, LLC

FDA Registered Facility

cleanyourdanghands.com

IG: @thehandsanitizercompany

#CLEANYOURDANGHANDS

OPEN SQUEEZE SANITIZE!

USE FOR YOUR REFILLABLE HAND SANITIZER PRODUCTS!